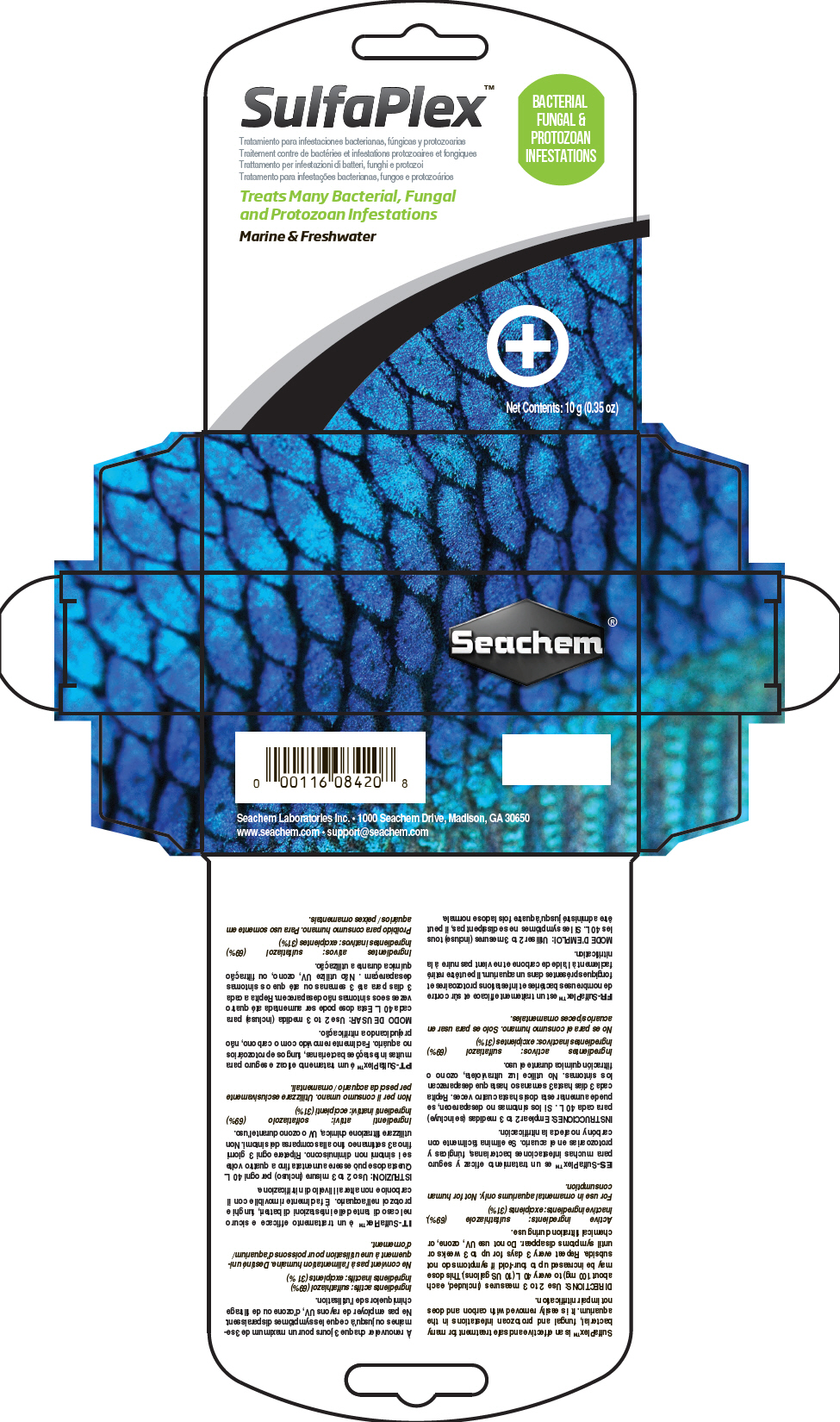 DRUG LABEL: Sulfaplex
NDC: 55999-085 | Form: POWDER
Manufacturer: Seachem Laboratories Inc.
Category: animal | Type: OTC ANIMAL DRUG LABEL
Date: 20180716

ACTIVE INGREDIENTS: Sulfathiazole 694 mg/1 g

Sulfaplex™

VETERINARY INDICATIONS

SulfaPlex™ is an effective and safe treatment for many bacterial, fungal and protozoan infestations in the aquarium. It is easily removed with carbon and does not impair nitrification.

DOSAGE AND ADMINISTRATION

DIRECTIONS: Use 2 to 3 measures (included, each about 100 mg) to every 40 L (10 US gallons).This dose may be increased up to four-fold if symptoms do not subside. Repeat every 3 days for up to 3 weeks or until symptoms disappear. Do not use UV, ozone, or chemical filtration during use.

Active ingredients: sulfathiazole (69%).

Inactive ingredients: excipients (31%)

SAFE HANDLING WARNING

For use in ornamental aquariums only. Not for human consumption.

Seachem Laboratories Inc. • 1000 Seachem Drive, Madison, GA 30650

www.seachem.com • support@seachem.com

PRINCIPAL DISPLAY PANEL - 10 g Vial Carton

SulfaPlex™

BACTERIAL
FUNGAL &
PROTOZOAN
INFESTATIONS

Treats Many Bacterial, Fungal
and Protozoan Infestations

Marine & Freshwater

Net Contents: 10 g (0.35 oz)

Seachem®